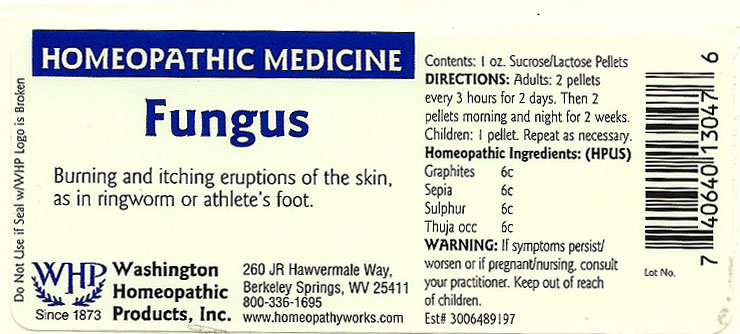 DRUG LABEL: Fungus
NDC: 68428-009 | Form: PELLET
Manufacturer: Washington Homeopathic Products
Category: homeopathic | Type: HUMAN OTC DRUG LABEL
Date: 20191223

ACTIVE INGREDIENTS: GRAPHITE 6 [hp_C]/28 g; SEPIA OFFICINALIS JUICE 6 [hp_C]/28 g; SULFUR 6 [hp_C]/28 g; THUJA OCCIDENTALIS LEAFY TWIG 6 [hp_C]/28 g
INACTIVE INGREDIENTS: SUCROSE; LACTOSE

DRUG FACTS

ACTIVE INGREDIENTS

GRAPHITES 6C

SEPIA 6C

SULPHUR 6C

THUJA 6C

USES

To relieve the symptoms of burning and itching eruptions of the skin, as in ringworm or athlete’s foot.

KEEP OUT OF REACH OF CHILDREN

Keep this and all medicines out of reach of children.

INDICATIONS

GRAPHITES Cracks in skin

SEPIA Indifference

SULPHUR Skin problems

THUJA Warts

STOP USE AND ASK DOCTOR

If symptoms persist/worsen or if pregnant/nursing, stop use and consult your practitioner.

DIRECTIONS

Adults 2 pellets every 3 hours for 2 days. Then 2 pellets morning and night for 2 weeks.

Children: 1 pellet. Repeat as necessary.

INACTIVE INGREDIENTS

Sucrose/Lactose

PRINCIPAL DISPLAY PANEL

Enter section text here